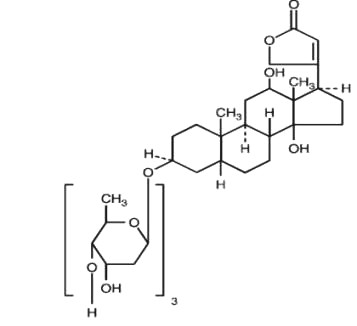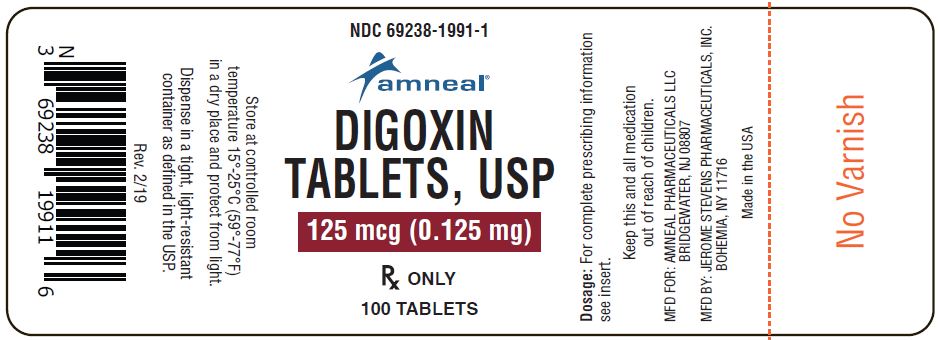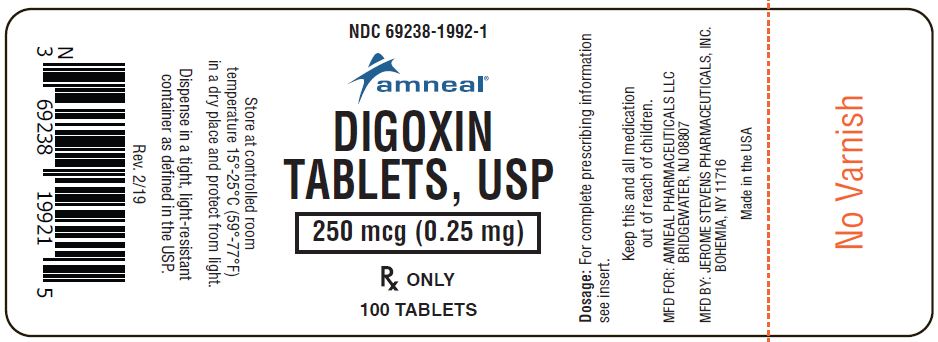 DRUG LABEL: Digoxin
NDC: 69238-1991 | Form: TABLET
Manufacturer: Amneal Pharmaceuticals NY LLC
Category: prescription | Type: HUMAN PRESCRIPTION DRUG LABEL
Date: 20231229

ACTIVE INGREDIENTS: DIGOXIN 125 ug/1 1
INACTIVE INGREDIENTS: SILICON DIOXIDE; CROSCARMELLOSE SODIUM; D&C YELLOW NO. 10; ALUMINUM OXIDE; ANHYDROUS LACTOSE; MAGNESIUM STEARATE; CELLULOSE, MICROCRYSTALLINE; STEARIC ACID

Digoxin Tablets, USP
125 mcg (0.125 mg)
250 mcg (0.25 mg)

DESCRIPTION

Digoxin is one of the cardiac (or digitalis) glycosides, a closely related group of drugs having in common specific effects on the myocardium. These drugs are found in a number of plants. Digoxin is extracted from the leaves of Digitalis lanata. The term “digitalis” is used to designate the whole group of glycosides. The glycosides are composed of two portions: a sugar and a cardenolide (hence “glycosides”).

Digoxin is described chemically as (3β,5β,12β)-3-[(0-2,6-dideoxy-β-D-ribo-hexopyranosyl-(1→4)-0-2,6-dideoxy-β-D-ribo-hexopyranosyl-(1→4)-2,6-dideoxy-β-D-ribo-hexopyranosyl)oxy]-12,14-dihydroxy-card-20(22)-enolide. Its molecular formula is C41H64O14, its molecular weight is 780.95, and its structural formula is:

Digoxin exists as odorless white crystals that melt with decomposition above 230°C. The drug is practically insoluble in water and in ether; slightly soluble in diluted (50%) alcohol and in chloroform; and freely soluble in pyridine.

Digoxin is supplied as 125 mcg (0.125 mg) or 250 mcg (0.25 mg) tablets for oral administration. Each tablet contains the labeled amount of digoxin USP and the following inactive ingredients: 0.250 mg - colloidal silicon dioxide, croscarmellose sodium, lactose anhydrous, magnesium stearate, microcrystalline cellulose, stearic acid.

0.125 mg - colloidal silicon dioxide, croscarmellose sodium, D&C yellow aluminum lake #10, lactose anhydrous, magnesium stearate, microcrystalline cellulose, stearic acid.

CLINICAL PHARMACOLOGY

Mechanism of Action

Digoxin inhibits sodium-potassium ATPase, an enzyme that regulates the quantity of sodium and potassium inside cells. Inhibition of the enzyme leads to an increase in the intracellular concentration of sodium and thus (by stimulation of sodium-calcium exchange) an increase in the intracellular concentration of calcium. The beneficial effects of digoxin result from direct actions on cardiac muscle, as well as indirect actions on the cardiovascular system mediated by effects on the autonomic nervous system. The autonomic effects include: (1) a vagomimetic action, which is responsible for the effects of digoxin on the sinoatrial and atrioventricular (AV) nodes; and (2) baroreceptor sensitization, which results in increased afferent inhibitory activity and reduced activity of the sympathetic nervous system and renin-angiotensin system for any given increment in mean arterial pressure. The pharmacologic consequences of these direct and indirect effects are: (1) an increase in the force and velocity of myocardial systolic contraction (positive inotropic action); (2) a decrease in the degree of activation of the sympathetic nervous system and renin-angiotensin system (neurohormonal deactivating effect); and (3) slowing of the heart rate and decreased conduction velocity through the AV node (vagomimetic effect). The effects of digoxin in heart failure are mediated by its positive inotropic and neurohormonal deactivating effects, whereas the effects of the drug in atrial arrhythmias are related to its vagomimetic actions. In high doses, digoxin increases sympathetic outflow from the central nervous system (CNS). This increase in sympathetic activity may be an important factor in digitalis toxicity.

Pharmacokinetics

Absorption:Following oral administration, peak serum concentrations of digoxin occur at 1 to 3 hours. Absorption of digoxin from digoxin tablets has been demonstrated to be 60% to 80% complete compared to an identical intravenous dose of digoxin (absolute bioavailability) or digoxin solution in capsules (relative bioavailability). When digoxin tablets are taken after meals, the rate of absorption is slowed, but the total amount of digoxin absorbed is usually unchanged. When taken with meals high in bran fiber, however, the amount absorbed from an oral dose may be reduced. Comparisons of the systemic availability and equivalent doses for oral preparations of digoxin are shown in Table 1:

Table 1: Comparisons of the Systemic Availability and Equivalent Doses for Oral Preparations of Digoxin
Product | Absolute Bioavailability | Equivalent Doses (mcg) [For example, 125 mcg Digoxin Tablets equivalent to 125 mcg Digoxin Elixir Pediatric equivalent to 100 mcg Digoxin Solution in Capsules equivalent to 100 mcg Digoxin Injection/IV.] Among Dosage Forms
Digoxin Tablets | 60-80% | 62.5 | 125 | 250 | 500
Digoxin Elixir Pediatric | 70-85% | 62.5 | 125 | 250 | 500
Digoxin Solution in Capsules | 90-100% | 50 | 100 | 200 | 400
Digoxin Injection/IV | 100% | 50 | 100 | 200 | 400

In some patients, orally administered digoxin is converted to inactive reduction products (e.g., dihydrodigoxin) by colonic bacteria in the gut. Data suggest that one in ten patients treated with digoxin tablets will degrade 40% or more of the ingested dose. As a result, certain antibiotics may increase the absorption of digoxin in such patients. Although inactivation of these bacteria by antibiotics is rapid, the serum digoxin concentration will rise at a rate consistent with the elimination half-life of digoxin. The magnitude of rise in serum digoxin concentration relates to the extent of bacterial inactivation, and may be as much as two-fold in some cases.

Distribution: Following drug administration, a 6- to 8-hour tissue distribution phase is observed. This is followed by a much more gradual decline in the serum concentration of the drug, which is dependent on the elimination of digoxin from the body. The peak height and slope of the early portion (absorption/distribution phases) of the serum concentration-time curve are dependent upon the route of administration and the absorption characteristics of the formulation. Clinical evidence indicates that the early high serum concentrations do not reflect the concentration of digoxin at its site of action, but that with chronic use, the steady-state post-distribution serum concentrations are in equilibrium with tissue concentrations and correlate with pharmacologic effects. In individual patients, these post-distribution serum concentrations may be useful in evaluating therapeutic and toxic effects (see DOSAGE AND ADMINISTRATION: Serum Digoxin Concentrations).

Digoxin is concentrated in tissues and therefore has a large apparent volume of distribution. Digoxin crosses both the blood-brain barrier and the placenta. At delivery, the serum digoxin concentration in the newborn is similar to the serum concentration in the mother. Approximately 25% of digoxin in the plasma is bound to protein. Serum digoxin concentrations are not significantly altered by large changes in fat tissue weight, so that its distribution space correlates best with lean (i.e., ideal) body weight, not total body weight.

Metabolism: Only a small percentage (16%) of a dose of digoxin is metabolized. The end metabolites, which include 3 β-digoxigenin, 3-keto-digoxigenin, and their glucuronide and sulfate conjugates, are polar in nature and are postulated to be formed via hydrolysis, oxidation, and conjugation. The metabolism of digoxin is not dependent upon the cytochrome P-450 system, and digoxin is not known to induce or inhibit the cytochrome P-450 system.

Excretion: Elimination of digoxin follows first-order kinetics (that is, the quantity of digoxin eliminated at any time is proportional to the total body content). Following intravenous administration to healthy volunteers, 50% to 70% of a digoxin dose is excreted unchanged in the urine. Renal excretion of digoxin is proportional to glomerular filtration rate and is largely independent of urine flow. In healthy volunteers with normal renal function, digoxin has a half-life of 1.5 to 2.0 days. The half- life in anuric patients is prolonged to 3.5 to 5 days. Digoxin is not effectively removed from the body by dialysis, exchange transfusion, or during cardiopulmonary bypass because most of the drug is bound to tissue and does not circulate in the blood.

Special Populations: Race differences in digoxin pharmacokinetics have not been formally studied. Because digoxin is primarily eliminated as unchanged drug via the kidney and because there are no important differences in creatinine clearance among races, pharmacokinetic differences due to race are not expected.

The clearance of digoxin can be primarily correlated with renal function as indicated by creatinine clearance. The Cockcroft and Gault formula for estimation of creatinine clearance includes age, body weight, and gender. Table 5 that provides the usual daily maintenance dose requirements of Digoxin Tablets based on creatinine clearance (per 70 kg) is presented in the DOSAGE AND ADMINISTRATION section.

Plasma digoxin concentration profiles in patients with acute hepatitis generally fell within the range of profiles in a group of healthy subjects.

Pharmacodynamic and Clinical Effects: The times to onset of pharmacologic effect and to peak effect of preparations of digoxin are shown in Table 2:

Table 2: Times to Onset of Pharmacologic Effect and to Peak Effect of Preparations of Digoxin
Product | Time to Onset of Effect [Documented for ventricular response rate in atrial fibrillation, inotropic effects and electrocardiographic changes.] | Time to Peak Effect [Depending upon rate of infusion.]
Digoxin Tablets | 0.5 - 2 hours | 2 - 6 hours
Digoxin Elixir Pediatric | 0.5 - 2 hours | 2 - 6 hours
Digoxin Solution in Capsules | 0.5 - 2 hours | 2 - 6 hours
Digoxin Injection/IV | 5 - 30 minutes | 1 - 4 hours

Hemodynamic Effects: Digoxin produces hemodynamic improvement in patients with heart failure. Short- and long-term therapy with the drug increases cardiac output and lowers pulmonary artery pressure, pulmonary capillary wedge pressure, and systemic vascular resistance. These hemodynamic effects are accompanied by an increase in the left ventricular ejection fraction and a decrease in end-systolic and end-diastolic dimensions.

Chronic Heart Failure: Two 12-week, double-blind, placebo-controlled studies enrolled 178 (RADIANCE trial) and 88 (PROVED trial) patients with NYHA class II or III heart failure previously treated with digoxin, a diuretic, and an ACE inhibitor (RADIANCE only) and randomized them to placebo or treatment with digoxin. Both trials demonstrated better preservation of exercise capacity in patients randomized to digoxin. Continued treatment with digoxin reduced the risk of developing worsening heart failure, as evidenced by heart failure-related hospitalizations and emergency care and the need for concomitant heart failure therapy. The larger study also showed treatment-related benefits in NYHA class and patients’ global assessment. In the smaller trial, these trended in favor of a treatment benefit.

The Digitalis Investigation Group (DIG) main trial was a multicenter, randomized, double-blind, placebo-controlled mortality study of 6801 patients with heart failure and left ventricular ejection fraction ≤0.45. At randomization, 67% were NYHA class I or II, 71% had heart failure of ischemic etiology, 44% had been receiving digoxin, and most were receiving concomitant ACE inhibitor (94%) and diuretic (82%). Patients were randomized to placebo or Digoxin, the dose of which was adjusted for the patient’s age, sex, lean body weight, and serum creatinine (see DOSAGE AND ADMINISTRATION), and followed for up to 58 months (median 37 months). The median daily dose prescribed was 0.25 mg. Overall all-cause mortality was 35% with no difference between groups (95% confidence limits for relative risk of 0.91 to 1.07). Digoxin was associated with a 25% reduction in the number of hospitalizations for heart failure, a 28% reduction in the risk of a patient having at least one hospitalization for heart failure, and a 6.5% reduction in total hospitalizations (for any cause).

Use of digoxin was associated with a trend to increase time to all-cause death or hospitalization. The trend was evident in subgroups of patients with mild heart failure as well as more severe disease, as shown in Table 3. Although the effect on all-cause death or hospitalization was not statistically significant, much of the apparent benefit derived from effects on mortality and hospitalization attributed to heart failure.

Table 3: Subgroup Analyses of Mortality and Hospitalization During the First Two Years Following Randomization
 |  | Risk of All-Cause Mortality or All-Cause Hospitalization [Number of patients with an event during the first 2 years per 1000 randomized patients.]
 | n | Placebo | Digoxin | Relative risk [Relative risk (95% confidence interval).]
All patients (EF ≤0.45) | 6801 | 604 | 593 | 0.94 (0.88-1.00)
NYHA I/II EF 0.25-0.45 CTR ≤0.55 | 4571 4543 4455 | 549 568 561 | 541 571 563 | 0.96 (0.89-1.04) 0.99 (0.91-1.07) 0.98 (0.91-1.06)
NYHA III/IV EF <0.25 CTR >0.55 | 2224 2258 2346 | 719 677 687 | 696 637 650 | 0.88 (0.80-0.97) 0.84 (0.76-0.93) 0.85 (0.77-0.94)
EF >0.45 [DIG Ancillary Study.] | 987 | 571 | 585 | 1.04 (0.88-1.23)
 |  | Risk of HF-Related Mortality or HF-Related Hospitalization
 | n | Placebo | Digoxin | Relative risk
All patients (EF ≤0.45) | 6801 | 294 | 217 | 0.69 (0.63-0.76)
NYHA I/II EF 0.25-0.45 CTR ≤0.55 | 4571 4543 4455 | 242 244 239 | 178 190 180 | 0.70 (0.62-0.80) 0.74 (0.66-.084) 0.71 (0.63-0.81)
NYHA III/IV EF <0.25 CTR >0.55 | 2224 2258 2346 | 402 394 398 | 295 270 287 | 0.65 (0.57-0.75) 0.61 (0.53-0.71) 0.65 (0.57-0.75)
EF >0.45 | 987 | 179 | 136 | 0.72 (0.53-0.99)

In situations where there is no statistically significant benefit of treatment evident from a trial’s primary endpoint, results pertaining to a secondary endpoint should be interpreted cautiously.

Chronic Atrial Fibrillation: In patients with chronic atrial fibrillation, digoxin slows rapid ventricular response rate in a linear dose-response fashion from 0.25 to 0.75 mg/day. Digoxin should not be used for the treatment of multifocal atrial tachycardia.

INDICATIONS AND USAGE

Heart Failure: Digoxin is indicated for the treatment of mild to moderate heart failure. Digoxin increases left ventricular ejection fraction and improves heart failure symptoms as evidenced by exercise capacity and heart failure symptoms as evidenced by exercise capacity and heart failure-related hospitalizations and emergency care, while having no effect on mortality. Where possible, digoxin should be used with a diuretic and an angiotensin-converting enzyme inhibitor, but an optimal order for starting these three drugs cannot be specified.

Atrial Fibrillation: Digoxin is indicated for the control of ventricular response rate in patients with chronic atrial fibrillation.

CONTRAINDICATIONS

Digitalis glycosides are contraindicated in patients with ventricular fibrillation or in patients with a known hypersensitivity to digoxin. A hypersensitivity reaction to other digitalis preparations usually constitutes a contraindication to digoxin.

WARNINGS

Sinus Node Disease and AV Block: Because digoxin slows sinoatrial and AV conduction, the drug commonly prolongs the PR interval. The drug may cause severe sinus bradycardia or sinoatrial block in patients with pre-existing sinus node disease and may cause advanced or complete heart block in patients with pre-existing incomplete AV block. In such patients consideration should be given to the insertion of a pacemaker before treatment with digoxin.

Accessory AV Pathway (Wolff-Parkinson-White Syndrome): After intravenous digoxin therapy, some patients with paroxysmal atrial fibrillation or flutter and a coexisting accessory AV pathway have developed increased antegrade conduction across the accessory pathway bypassing the Av node, leading to a very rapid ventricular response or ventricular fibrillation. Unless conduction down the accessory pathway has been blocked (either pharmacologically or by surgery), digoxin should not be used in such patients. The treatment of paroxysmal supraventricular tachycardia in such patients is usually direct-current cardioversion.

Use in Patients with Preserved Left Ventricular Systolic Function: Patients with certain disorders involving heart failure associated with preserved left ventricular ejection fraction may be particularly susceptible to toxicity of the drug. Such disorders include restrictive cardiomyopathy, constrictive pericarditis, amyloid heart disease, and acute cor pulmonale. Patients with idiopathic hypertrophic subaortic stenosis may have worsening of the outflow obstruction due to the inotropic effects of digoxin.

PRECAUTIONS

Use in Patients with Impaired Renal Function: Digoxin is primarily excreted by the kidneys; therefore, patients with impaired renal function require smaller than usual maintenance doses of digoxin (see DOSAGE AND ADMINISTRATION). Because of the prolonged elimination half-life, a longer period of time is required to achieve an initial or new steady-state serum concentration in patients with renal impairment than in patients with normal renal function. If appropriate care is not taken to reduce the dose of digoxin, such patients are at high risk for toxicity, and toxic effects will last longer in such patients than in patients with normal renal function.

Use in Patients with Electrolyte Disorders: In patients with hypokalemia or hypomagnesemia, toxicity may occur despite serum digoxin concentrations below 2.0 ng/mL, because potassium or magnesium depletion sensitizes the myocardium to digoxin. Therefore, it is desirable to maintain normal serum potassium and magnesium concentrations in patients being treated with digoxin. Deficiencies of these electrolytes may result from malnutrition, diarrhea, or prolonged vomiting, as well as the use of the following drugs or procedures: diuretics, amphotericin B, corticosteroids, antacids, dialysis, and mechanical suction of gastrointestinal secretions.

Hypercalcemia from any cause predisposes the patient to digitalis toxicity. Calcium, particularly when administered rapidly by the intravenous route, may produce serious arrhythmias in digitalized patients. On the other hand, hypocalcemia can nullify the effects of digoxin in humans; thus, digoxin may be ineffective until serum calcium is restored to normal. These interactions are related to the fact that digoxin affects contractility and excitability of the heart in a manner similar to that of calcium.

Use in Thyroid Disorders and Hypermetabolic States: Hypothyroidism may reduce the requirements for digoxin. Heart failure and/or atrial arrhythmias resulting from hypermetabolic or hyperdynamic states (e.g., hyperthyroidism, hypoxia, or arteriovenous shunt) are best treated by addressing the underlying condition. Atrial arrhythmias associated with hypermetabolic states are particularly resistant to digoxin treatment. Care must be taken to avoid toxicity if digoxin is used.

Use in Patients with Acute Myocardial Infarction: Digoxin should be used with caution in patients with acute myocardial infarction. The use of inotropic drugs in some patients in this setting may result in undesirable increases in myocardial oxygen demand and ischemia.

Use During Electrical Cardioversion: It may be desirable to reduce the dose of digoxin for 1 to 2 days prior to electrical cardioversion of atrial fibrillation to avoid the induction of ventricular arrhythmias, but physicians must consider the consequences of increasing the ventricular response if digoxin is withdrawn. If digitalis toxicity is suspected, elective cardioversion should be delayed. If it is not prudent to delay cardioversion, the lowest possible energy level should be selected to avoid provoking ventricular arrhythmias.

Laboratory Test Monitoring

Patients receiving digoxin should have their serum electrolytes and renal function (serum creatinine concentrations) assessed periodically; the frequency of assessments will depend on the clinical setting. For discussion of serum digoxin concentrations, see DOSAGE AND ADMINISTRATION section.

Drug Interactions

Potassium-depleting diuretics are a major contributing factor to digitalis toxicity. Calcium, particularly if administered rapidly by the intravenous route, may produce serious arrhythmias in digitalized patients. Quinidine, verapamil, amiodarone, propafenone, indomethacin, itraconazole, alprazolam, and spironolactone raise the serum digoxin concentration due to a reduction in clearance and/or in volume of distribution of the drug, with the implication that digitalis intoxication may result. Erythromycin and clarithromycin (and possibly other macrolide antibiotics) and tetracycline may increase digoxin absorption in patients who inactivate digoxin by bacterial metabolism in the lower intestine, so that digitalis intoxication may result (see CLINICAL PHARMACOLOGY: Absorption). Propantheline and diphenoxylate, by decreasing gut motility, may increase digoxin absorption. Antacids, kaolin-pectin, sulfasalazine, neomycin, cholestyramine, certain anticancer drugs, and metoclopramide may interfere with intestinal digoxin absorption, resulting in unexpectedly low serum concentrations. Rifampin may decrease serum digoxin concentration, especially in patients with renal dysfunction, by increasing the non-renal clearance of digoxin. There have been inconsistent reports regarding the effects of other drugs [e.g., quinine, penicillamine] on serum digoxin concentration. Thyroid administration to a digitalized, hypothyroid patient may increase the dose requirement of digoxin. Concomitant use of digoxin and sympathomimetics increases the risk of cardiac arrhythmias. Succinylcholine may cause a sudden extrusion of potassium from muscle cells, and may thereby cause arrhythmias in digitalized patients. Although beta-adrenergic blockers or calcium channel blockers and digoxin may be useful in combination to control atrial fibrillation, their additive effects on AV node conduction can result in advanced or complete heart block.

Due to the considerable variability of these interactions, the dosage of digoxin should be individualized when patients receive these medications concurrently. Furthermore, caution should be exercised when combining digoxin with any drug that may cause a significant deterioration in renal function, since a decline in glomerular filtration or tubular secretion may impair the excretion of digoxin.

Drug/Laboratory Test Interactions

The use of therapeutic doses of digoxin may cause prolongation of the PR interval and depression of the ST segment on the electrocardiogram. Digoxin may produce false positive ST-T changes on the electrocardiogram during exercise testing. These electrophysiologic effects reflect an expected effect of the drug and are not indicative of toxicity.

Carcinogenesis, Mutagenesis, Impairment of Fertility

There have been no long-term studies performed in animals to evaluate carcinogenic potential, nor have studies been conducted to assess the mutagenic potential of digoxin or its potential to affect fertility.

Pregnancy

Teratogenic Effects

Pregnancy Category C. Animal reproduction studies have not been conducted with digoxin. It is also not known whether digoxin can cause fetal harm when administered to a pregnant woman or can affect reproductive capacity. Digoxin should be given to a pregnant woman only if clearly needed.

Nursing Mothers

Studies have shown that digoxin concentrations in the mother’s serum and milk are similar. However, the estimated exposure of a nursing infant to digoxin via breast feeding will be far below the usual infant maintenance dose. Therefore, this amount should have no pharmacologic effect upon the infant. Nevertheless, caution should be exercised when digoxin is administered to a nursing woman.

Pediatric Use

Newborn infants display considerable variability in their tolerance to digoxin. Premature and immature infants are particularly sensitive to the effects of digoxin, and the dosage of the drug must not only be reduced but must be individualized according to their degree of maturity. Digitalis glycosides can cause poisoning in children due to accidental ingestion.

Geriatric Use

The majority of clinical experience gained with digoxin has been in the elderly population. This experience has not identified differences in response or adverse effects between the elderly and younger patients. However, this drug is known to be substantially excreted by the kidney, and the risk of toxic reactions to this drug may be greater in patients with impaired renal function. Because elderly patients are more likely to have decreased renal function, care should be taken in dose selection, which should be based on renal function, and it may be useful to monitor renal function (see DOSAGE AND ADMINISTRATION).

ADVERSE REACTIONS

In general, the adverse reactions of digoxin are dose-dependent and occur at doses higher than those needed to achieve a therapeutic effect. Hence, adverse reactions are less common when digoxin is used within the recommended dose range or therapeutic serum concentration range and when there is careful attention to concurrent medications and conditions.

Because some patients may be particularly susceptible to side effects with digoxin, the dosage of the drug should always be selected carefully and adjusted as the clinical condition of the patient warrants. In the past, when high doses of digoxin were used and little attention was paid to clinical status or concurrent medications, adverse reactions to digoxin were more frequent and severe. Cardiac adverse reactions accounted for about one-half, gastrointestinal disturbances for about one-fourth, and CNS and other toxicity for about one-fourth of these adverse reactions. However, available evidence suggests that the incidence and severity of digoxin toxicity has decreased substantially in recent years. In recent controlled clinical trials, in patients with predominantly mild to moderate heart failure, the incidence of adverse experiences was comparable in patients taking digoxin and in those taking placebo. In a large mortality trial, the incidence of hospitalization for suspected digoxin toxicity was 2% in patients taking digoxin compared to 0.9% in patients taking placebo. In this trial, the most common manifestations of digoxin toxicity included gastrointestinal and cardiac disturbances; CNS manifestations were less common.

Adults: Cardiac: Therapeutic doses of digoxin may cause heart block in patients with pre-existing sinoatrial or AV conduction disorders; heart block can be avoided by adjusting the dose of digoxin. Prophylactic use of a cardiac pacemaker may be considered if the risk of heart block is considered unacceptable. High doses of digoxin may produce a variety of rhythm disturbances, such as first-degree, second-degree (Wenckebach), or third-degree heart block (including asystole); atrial tachycardia with block; AV dissociation; accelerated junctional (nodal) rhythm; unifocal or multiform ventricular premature contractions (especially bigeminy or trigeminy); ventricular tachycardia; and ventricular fibrillation. Digoxin produces PR prolongation and ST segment depression which should not by themselves be considered digoxin toxicity. Cardiac toxicity can also occur at therapeutic doses in patients who have conditions which may alter their sensitivity to digoxin (see WARNINGS and PRECAUTIONS).

Gastrointestinal: Digoxin may cause anorexia, nausea, vomiting, and diarrhea. Rarely, the use of digoxin has been associated with abdominal pain, intestinal ischemia, and hemorrhagic necrosis of the intestines.

CNS: Digoxin can produce visual disturbances (blurred or yellow vision), headache, weakness, dizziness, apathy, confusion, and mental disturbances (such as anxiety, depression, delirium, and hallucination).

Other: Gynecomastia has been occasionally observed following the prolonged use of digoxin. Thrombocytopenia and maculopapular rash
and other skin reactions have been rarely observed.

Table 4 summarizes the incidence of those adverse experiences listed above for patients treated with digoxin tablets or placebo from two randomized, double-blind, placebo-controlled withdrawal trials. Patients in these trials were also receiving diuretics with or without angiotensin-converting enzyme inhibitors. These patients had been stable on digoxin, and were randomized to digoxin or placebo. The results shown in Table 4 reflect the experience in patients following dosage titration with the use of serum digoxin concentrations and careful follow-up. These adverse experiences are consistent with results from a large, placebo-controlled mortality trial (DIG trial) wherein over half the patients were not receiving digoxin prior to enrollment.

Table 4: Adverse Experiences in Two Parallel, Double-Blind, Placebo-Controlled Withdrawal Trials (Number of Patients Reporting)
Adverse Experience | Digoxin Patients (n = 123) | Placebo Patients (n = 125)
Cardiac Palpitation Ventricular extrasystole Tachycardia Heart arrest | 1 1 2 1 | 4 1 1 1
Gastrointestinal Anorexia Nausea Vomiting Diarrhea Abdominal pain | 1 4 2 4 0 | 4 2 1 1 6
CNS Headache Dizziness Mental disturbances | 4 6 5 | 4 5 1
Other Rash Death | 2 4 | 1 3

Infants and Children: The side effects of digoxin in infants and children differ from those seen in adults in several respects. Although digoxin may produce anorexia, nausea, vomiting, diarrhea, and CNS disturbances in young patients, these are rarely the initial symptoms of overdosage. Rather, the earliest and most frequent manifestation of excessive dosing with digoxin in infants and children is the appearance of cardiac arrhythmias, including sinus bradycardia. In children, the use of digoxin may produce any arrhythmia. The most common are conduction disturbances or supraventricular tachyarrhythmias, such as atrial tachycardia (with or without block) and junctional (nodal) tachycardia. Ventricular arrhythmias are less common. Sinus bradycardia may be a sign of impending digoxin intoxication, especially in infants, even in the absence of first-degree heart block. Any arrhythmia or alteration in cardiac conduction that develops in a child taking digoxin should be assumed to be caused by digoxin, until further evaluation proves otherwise.

OVERDOSAGE

Treatment of Adverse Reactions Produced by Overdosage: Digoxin should be temporarily discontinued until the adverse reaction resolves. Every effort should also be made to correct factors that may contribute to the adverse reaction (such as electrolyte disturbances or concurrent medications). Once the adverse reaction has resolved, therapy with digoxin may be reinstituted, following a careful reassessment of dose.

Withdrawal of digoxin may be all that is required to treat the adverse reaction. However, when the primary manifestation of digoxin overdosage is a cardiac arrhythmia, additional therapy may be needed.

If the rhythm disturbance is a symptomatic bradyarrhythmia or heart block, consideration should be given to the reversal of toxicity with DIGIBIND® [Digoxin Immune Fab (Ovine)] (see Massive Digitalis Overdosage subsection), the use of atropine, or the insertion of a temporary cardiac pacemaker. However, asymptomatic bradycardia or heart block related to digoxin may require only temporary withdrawal of the drug and cardiac monitoring of the patient.

If the rhythm disturbance is a ventricular arrhythmia, consideration should be given to the correction of electrolyte disorders, particularly if hypokalemia (see Administration of Potassium subsection) or hypomagnesemia is present. DIGIBIND is a specific antidote for digoxin and may be used to reverse potentially life-threatening ventricular arrhythmias due to digoxin overdosage.

Administration of Potassium: Every effort should be made to maintain the serum potassium concentration between 4.0 and 5.5 mmol/L. Potassium is usually administered orally, but when correction of the arrhythmia is urgent and the serum potassium concentration is low, potassium may be administered cautiously by the intravenous route. The electrocardiogram should be monitored for any evidence of potassium toxicity (e.g., peaking of T waves) and to observe the effect on the arrhythmia. Potassium salts may be dangerous in patients who manifest bradycardia or heart block due to digoxin (unless primarily related to supraventricular tachycardia) and in the setting of massive digitalis overdosage (see Massive Digitalis Overdosage subsection).

Massive Digitalis Overdosage: Manifestations of life-threatening toxicity include ventricular tachycardia or ventricular fibrillation, or progressive bradyarrhythmias, or heart block. The administration of more than 10 mg of digoxin in a previously healthy adult, or more than 4 mg in a previously healthy child, or a steady-state serum concentration greater than 10 ng/mL often results in cardiac arrest.

DIGIBIND should be used to reverse the toxic effects of ingestion of a massive overdose. The decision to administer DIGIBIND to a patient who has ingested a massive dose of digoxin but who has not yet manifested life-threatening toxicity should depend on the likelihood that life-threatening toxicity will occur (see above).

Patients with massive digitalis ingestion should receive large doses of activated charcoal to prevent absorption and bind digoxin in the gut during enteroenteric recirculation. Emesis or gastric lavage may be indicated especially if ingestion has occurred withing 30 minutes of the patient’s presentation at the hospital. Emesis should not be induced in patients who are obtunded. If a patient presents more than 2 hours after ingestion or already has toxic manifestations, it may be unsafe to induce vomiting or attempt passage of a gastric tube, because such maneuvers may induce an acute vagal episode that can worsen digitalis-related arrhythmias.

Severe digitalis intoxication can cause a massive shift of potassium from inside to outside the cell, leading to life-threatening hyperkalemia. The administration of potassium supplements in the setting of massive intoxication may be hazardous and should be avoided. Hyperkalemia caused be massive digitalis toxicity is best treated with DIGIBIND; initial treatment with glucose and insulin may also be required if hyperkalemia itself is acutely life-threatening.

DOSAGE AND ADMINISTRATION

General: Recommended dosages of digoxin may require considerable modification because of individual sensitivity of the patient to the drug, the presence of associated conditions, or the use of concurrent medications. In selecting a dose of digoxin, the following factors must be considered:

1. The body weight of the patient. Doses should be calculated based upon lean (i.e., ideal) body weight.
2. The patient’s renal function, preferably evaluated on the basis of estimated creatinine clearance.
3. The patient’s age. Infants and children require different doses of digoxin than adults. Also, advanced age may be indicative of diminished renal function even in patients with normal serum creatinine concentration (i.e., below 1.5 mg/dL).
4. Concomitant disease states, concurrent medications, or other factors likely to alter the pharmacokinetic or pharmacodynamic profile of digoxin (see PRECAUTIONS).

Serum Digoxin Concentrations: In general, the dose of digoxin used should be determined on clinical grounds. However, measurement of serum digoxin concentrations can be helpful to the clinician in determining the adequacy of digoxin therapy and in assigning certain probabilities to the likelihood of digoxin intoxication. About two-thirds of adults considered adequately digitalized (without evidence of toxicity) have serum digoxin concentrations ranging from 0.8 to 2.0 ng/mL. However, digoxin may produce clinical benefits even at serum concentrations below this range. About two-thirds of adult patients with clinical toxicity have serum digoxin concentrations greater than 2.0 ng/mL. However, since one-third of patients with clinical toxicity have concentrations less than 2.0 ng/mL, values below 2.0 ng/mL do not rule out the possibility that a certain sign or symptom is related to digoxin therapy. Rarely, there are patients who are unable to tolerate digoxin at serum concentrations below 0.8 ng/mL. Consequently, the serum concentration of digoxin should always be interpreted in the overall clinical context, and an isolated measurement should not be used alone as the basis for increasing or decreasing the dose of the drug.

To allow adequate time for equilibration of digoxin between serum and tissue, sampling of serum concentrations should be done just before the next scheduled dose of the drug. If this is not possible, sampling should be done at least 6 to 8 hours after the last dose, regardless of the route of administration or the formulation used. On a once-daily dosing schedule, the concentration of digoxin will be 10% to 25% lower when sampled at 24 versus 8 hours, depending upon the patient’s renal function. On a twice-daily dosing schedule, there will be only minor differences in serum digoxin concentrations whether sampling is done at 8 or 12 hours after a dose.

If a discrepancy exists between the reported serum concentration and the observed clinical response, the clinician should consider the following possibilities:

1. Analytical problems in the assay procedure.
2. Inappropriate serum sampling time.
3. Administration of a digitalis glycoside other than digoxin
4. Conditions (described in WARNINGS and PRECAUTIONS) causing an alteration in the sensitivity of the patient to digoxin.
5. Serum digoxin concentration may decrease acutely during periods of exercise without any associated change in clinical efficacy due to increased binding of digoxin to skeletal muscle.

Heart Failure: Adults: Digitalization may be accomplished by either of two general approaches that vary in dosage and frequency of administration, but reach the same endpoint in terms of total amount of digoxin accumulated in the body.

1. If rapid digitalization is considered medically appropriate, it may be achieved by administering a loading dose based upon projected peak digoxin body stores. Maintenance dose can be calculated as a percentage of the loading dose.
2. More gradual digitalization may be obtained by beginning an appropriate maintenance dose, thus allowing digoxin body stores to accumulate slowly. Steady-state serum digoxin concentrations will be achieved in approximately five half-lives of the drug for the individual patient. Depending upon the patient's renal function, this will take between 1 and 3 weeks.

Rapid Digitalization with a Loading Dose: Peak digoxin body stores of 8 to 12 mcg/kg should provide therapeutic effect with minimum risk of toxicity in most patients with heart failure and normal sinus rhythm. Because of altered digoxin distribution and elimination, projected peak body stores for patients with renal insufficiency should be conservative (i.e., 6 to 10 mcg/kg) [see PRECAUTIONS].

The loading dose should be administered in several portions, with roughly half the total given as the first dose. Additional fractions of this planned total dose may be given at 6 to 8-hour intervals, with careful assessment of clinical response before each additional dose.

If the patient’s clinical response necessitates a change from the calculated loading dose of digoxin, then calculation of the maintenance dose should be based upon the amount actually given.

A single initial dose of 500 to 750 mcg (0.5 to 0.75 mg) of digoxin tablets usually produces a detectable effect in 0.5 to 2 hours that becomes maximal in 2 to 6 hours. Additional doses of 125 to 375 mcg (0.125 to 0.375 mg) may be given cautiously at 6 to 8-hour intervals until clinical evidence of an adequate effect is noted. The usual amount of digoxin tablets that a 70 kg patient requires to achieve 8 to 12 mcg/kg peak body stores is 750 to 1250 mcg (0.75 to 1.25 mg).

Digoxin Injection is frequently used to achieve rapid digitalization, with conversion to digoxin tablets or digoxin solution in capsules for maintenance therapy. If patients are switched from intravenous to oral digoxin formulations, allowances must be made for differences in bioavailability when calculating maintenance dosages (see Table 1, CLINICAL PHARMACOLOGY).

Maintenance Dosing: The doses of digoxin used in controlled trials in patients with heart failure have ranged from 125 to 500 mcg (0.125 to 0.5 mg) once daily. In these studies, the digoxin dose has been generally titrated according to the patient’s age, lean body weight, and renal function. Therapy is generally initiated at a dose of 250 mcg (0.25 mg) once daily in patients under age 70 with good renal function, at a dose of 125 mcg (0.125 mg) once daily in patients over age 70 or with impaired renal function, and at a dose of 62.5 mcg (0.0625 mg) in patients with marked renal impairment. Doses may be increased every 2 weeks according to clinical response.

In a subset of approximately 1800 patients enrolled in the DIG trial (wherein dosing was based on an algorithm similar to that in Table 5) the mean (± SD) serum digoxin concentrations at 1 month and 12 months were 1.01 ± 0.47 ng/mL and 0.97 ± 0.43 ng/mL, respectively.

The maintenance dose should be based upon the percentage of the peak body stores lost each day through elimination. The following formula has had wide clinical use:

Maintenance Dose = Peak Body Stores (i.e., Loading Dose)
x % Daily Loss/100
Where: % Daily Loss = 14 + Ccr/5

(Ccr is creatinine clearance, corrected to 70 kg body weight or 1.73 m^2 body surface area.)

Table 5 provides average daily maintenance dose requirements of digoxin tablets for patients with heart failure based upon lean body weight and renal function:

Table 5: Usual Daily Maintenance Dose Requirements (mcg) of Digoxin for Estimated Peak Body Stores of 10 mcg/kg
 | Lean Body Weight
Corrected Ccr (mL/min per 70 kg) [Ccr is creatinine clearance, corrected to 70 kg body weight or 1.73 m^2 body surface area. For adults, if only serum creatinine concentrations (Scr) are available, a Ccr (corrected to 70 kg body weight) may be estimated in men as (140 - Age)/Scr. For women, this result should be multiplied by 0.85. Note: This equation cannot be used for estimating creatinine clearance in infants or children.] | kg 50 lb 110 |  | 60 132 | 70 154 | 80 176 | 90 198 | 100 220 | Number of Days Before Steady State Achieved [If no loading dose administered.]
0 | 62.5 [62.5 mcg = 0.0625 mg] |  | 125 | 125 | 125 | 187.5 | 187.5 | 22
10 | 125 |  | 125 | 125 | 187.5 | 187.5 | 187.5 | 19
20 | 125 |  | 125 | 187.5 | 187.5 | 187.5 | 250 | 16
30 | 125 |  | 187.5 | 187.5 | 187.5 | 250 | 250 | 14
40 | 125 |  | 187.5 | 187.5 | 250 | 250 | 250 | 13
50 | 187.5 |  | 187.5 | 250 | 250 | 250 | 250 | 12
60 | 187.5 |  | 187.5 | 250 | 250 | 250 | 375 | 11
70 | 187.5 |  | 250 | 250 | 250 | 250 | 375 | 10
80 | 187.5 |  | 250 | 250 | 250 | 375 | 375 | 9
90 | 187.5 |  | 250 | 250 | 250 | 375 | 500 | 8
100 | 250 |  | 250 | 250 | 375 | 375 | 500 | 7

Example: Based on Table 5, a patient in heart failure with an estimated lean body weight of 70 kg and a Ccr of 60 mL/min should be given a dose of 250 mcg (0.25 mg) daily of digoxin tablets, usually taken after the morning meal. If no loading dose is administered, steady-state serum concentrations in this patient should be anticipated at approximately 11 days.

Infants and Children: In general, divided daily dosing is recommended for infants and young children (under age 10). In the newborn period, renal clearance of digoxin is diminished and suitable dosage adjustments must be observed. This is especially pronounced in the premature infant. Beyond the immediate newborn period, children generally require proportionally larger doses than adults on the basis of body weight or body surface area. Children over 10 years of age require adult dosages in proportion to their body weight. Some researchers have suggested that infants and young children tolerate slightly higher serum concentrations than do adults.

Daily maintenance doses for each age group are given in Table 6 and should provide therapeutic effects with minimum risk of toxicity in most patients with heart failure and normal sinus rhythm. These recommendations assume the presence of normal renal function:

Table 6: Daily Maintenance Doses in Children with Normal Renal Function
Age | Daily Maintenance Dose (mcg/kg)
2 to 5 Years | 10 to 15
5 to 10 Years | 7 to 10
Over 10 Years | 3 to 5

In children with renal disease, digoxin must be carefully titrated based upon clinical response.

It cannot be overemphasized that both adult and pediatric dosage guidelines provided are based upon average patient response and substantial individual variation can be expected. Accordingly, ultimate dosage selection must be based upon clinical assessment of the patient.

Atrial Fibrillation: Peak digoxin body stores larger than the 8 to 12 mcg/kg required for most patients with heart failure and normal sinus rhythm have been used for control of ventricular rate in patients with atrial fibrillation. Doses of digoxin used for the treatment of chronic atrial fibrillation should be titrated to the minimum dose that achieves the desired ventricular rate control without causing undesirable side effects. Data are not available to establish the appropriate resting or exercise target rates that should be achieved.

Dosage Adjustment When Changing Preparations: The difference in bio-availability between Digoxin Injection or Digoxin Solution in Capsules and Digoxin Elixir Pediatric or Digoxin Tablets must be considered when changing patients from one dosage form to another.
Doses of 100 mcg (0.1 mg) and 200 mcg (0.2 mg) of Digoxin Solution in Capsules are approximately equivalent to 125 mcg (0.125 mg) and
250 mcg (0.25 mg) doses of Digoxin Tablets and Elixir Pediatric, respectively (see Table 1 in CLINICAL PHARMACOLOGY: Pharmacokinetics).

HOW SUPPLIED

Digoxin Tablets, USP, 125 mcg (0.125 mg), Scored I.D. Imprint JSP-544 (yellow): Bottles of 100 (NDC 69238-1991-1) and 1000 (NDC 69238-1991-7).

Digoxin Tablets, USP, 250 mcg (0.250 mg), Scored I.D. Imprint JSP-545 (white): Bottles of 100 (NDC 69238-1992-1) and 1000 (NDC 69238-1992-7).

Store at controlled room temperature 15°-25°C (59°-77°F) in a dry place and protect from light.

Dispense in a tight, light-resistant container as defined in the USP.

Rx ONLY

Distributed by:
Amneal Pharmaceuticals LLC
Bridgewater, NJ 08807

Manufactured by:
Jerome Stevens Pharmaceuticals, Inc.
Bohemia, NY 11716

Rev. 02/19

MG #45109

PRINCIPAL DISPLAY PANEL — 125 mcg Container Label

NDC 69238-1991-1

DIGOXIN TABLETS, USP

125 mcg (0.125mg)

Rx ONLY

100 TABLETS

PRINCIPAL DISPLAY PANEL — 250 mcg Container Label

NDC 69238-1992-1

DIGOXIN TABLETS, USP

250 mcg (0.25 mg)

Rx ONLY

100 TABLETS